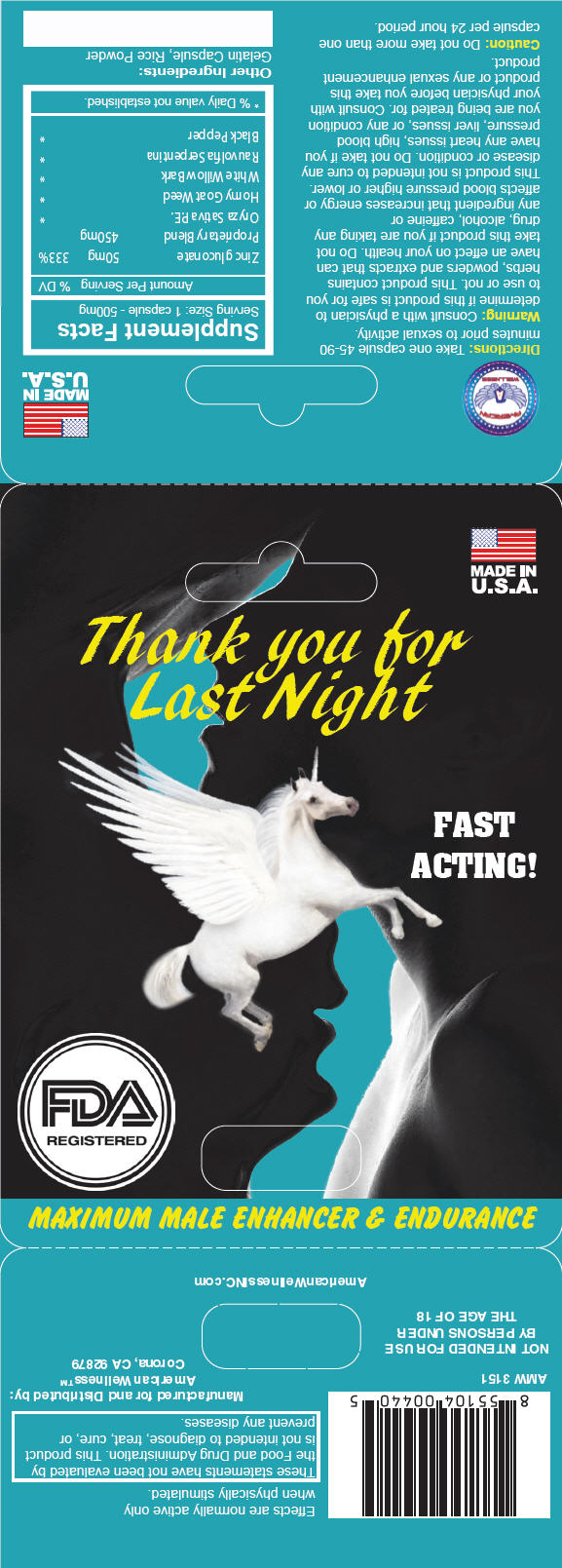 DRUG LABEL: Thank you for Last Night
NDC: 20146-1003 | Form: CAPSULE
Manufacturer: SAMSON PHARMACEUTICAL
Category: other | Type: DIETARY SUPPLEMENT
Date: 20171107

ACTIVE INGREDIENTS: Zinc Gluconate 50 mg/1 1
INACTIVE INGREDIENTS: Brown Rice; Epimedium Grandiflorum Top; Salix Alba Bark; Rauwolfia Serpentina; Black Pepper

Thank you for Last Night

Directions

Take one capsule 45-90 minutes prior to sexual activity.

Warning

Consult with a physician to determine if this product is safe for you to use or not. This product contains herbs, powders and extracts that can have an effect on your health. Do not take this product if you are taking any drug, alcohol, caffeine or any ingredient that increases energy or affects blood pressure higher or lower. This product is not intended to cure any disease or condition. Do not take if you have any heart issues, high blood pressure, liver issues, or any condition you are being treated for. Consult with your physician before you take this product or any sexual enhancement product.

Caution

Do not take more than one capsule per 24 hour period.

HEALTH CLAIM

Supplement Facts
Serving Size: 1 capsule - 500mg
Amount Per Serving |  | % DV
Zinc gluconate | 50mg | 333%
Proprietary Blend | 450mg
Oryza Sativa P.E. |  | [% Daily value not established.]
Horny Goat Weed
White Willow Bark
Rauvolfia Serpentina
Black Pepper

Other Ingredients

Gelatin Capsule, Rice Powder

HEALTH CLAIM

Manufactured for and Distributed by:
American Wellness™
Corona, CA 92879

PRINCIPAL DISPLAY PANEL - 1 Capsule Blister Pack Card

MADE IN
U.S.A.

Thank you for
Last Night

FAST
ACTING!

FDA
REGISTERED

MAXIMUM MALE ENHANCER & ENDURANCE